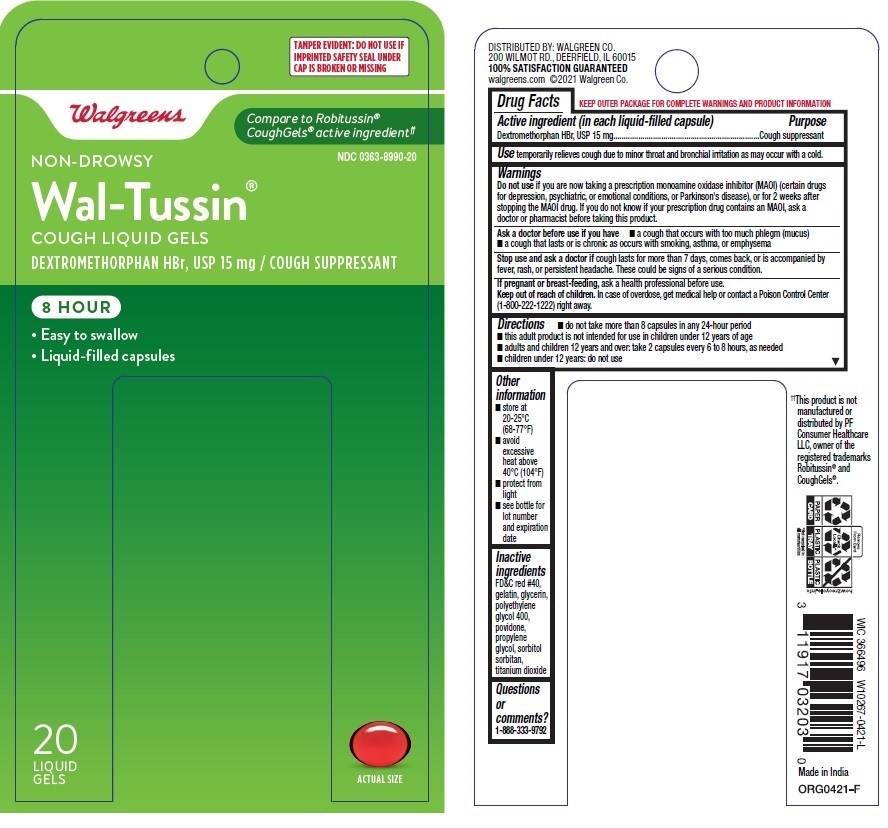 DRUG LABEL: Cough Relief
NDC: 0363-8990 | Form: CAPSULE, LIQUID FILLED
Manufacturer: WALGREEN COMPANY
Category: otc | Type: HUMAN OTC DRUG LABEL
Date: 20260116

ACTIVE INGREDIENTS: DEXTROMETHORPHAN HYDROBROMIDE 15 mg/1 1
INACTIVE INGREDIENTS: POLYETHYLENE GLYCOL 400; PROPYLENE GLYCOL; POVIDONE, UNSPECIFIED; WATER; GELATIN; GLYCERIN; SORBITOL; FD&C RED NO. 40; TITANIUM DIOXIDE

Walgreens Non-Drowsy Wal-Tussin Cough Liquid Gels

Drug Facts

Active ingredient (in each softgel)

Dextromethorphan HBr, USP 15mg

Purpose

Cough suppressant

Use

temporarily relieves cough due to minor throat and bronchial irritation as may occur with a cold.

Warnings

Do not use if you are now taking a prescription monoamine oxidase inhibitor (MAOI) (certain drugs for depression, psychiatric, or emotional conditions, or Parkinson's disease), or for 2 weeks after stopping the MAOI drug. If you do not know if your prescription drug contains an MAOI, ask a doctor or pharmacist before taking this product

Ask a doctor before use if you have

- a cough that occurs with too much phlegm (mucus)
- a cough that lasts or is chronic as occurs with smoking, asthma, or emphysema

Stop use and ask doctor if cough lasts for more than 7 days, comes back, or is accompanied by fever, rash, or persistent headache. These could be signs of a serious condition.

PREGNANCY OR BREAST FEEDING

If pregnant or breast-feeding, ask a health professional before use.

Keep out of reach of children. In case of overdose, get medical help orcontact a Poison Control Center right away. (1-800-222-1222)

Directions

- do not take more than 8 capsules in any 24-hour period
- this adult product is not intended for use in children under 12 years of age

adults and children 12 years and over | take 2 capsules every 6 to 8 hours, as needed
children under 12 years | do not use

Other information

- store at 20-25°C (68-77°F)
- avoid excessive heat above 40°C (104°F)
- protect from light

Inactive ingredients

FD&C Red No. 40, gelatin, glycerin, polyethylene glycol 400, propylene glycol, povidone, sorbitol sorbitan solution, titanium dioxide

Questions or comments?

1-888-333-9792

PRINCIPAL DISPLAY PANEL

Compare to Robitussin® Cough Gels® active ingredient*

Cough Relief

Dextromethorphan HBr 15mg

20 softgels